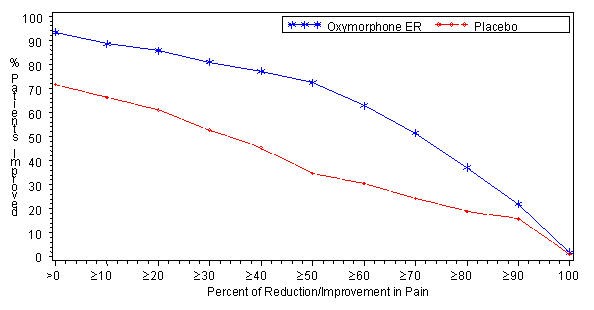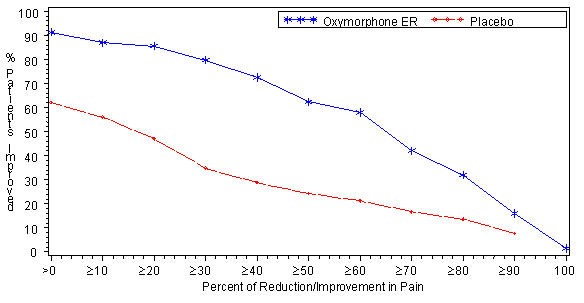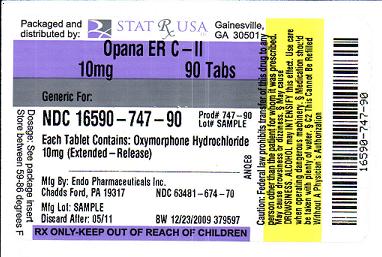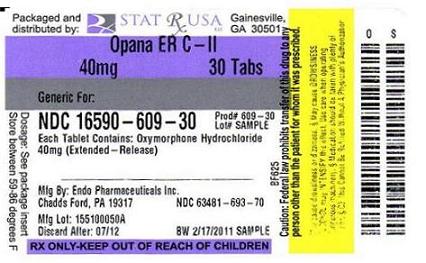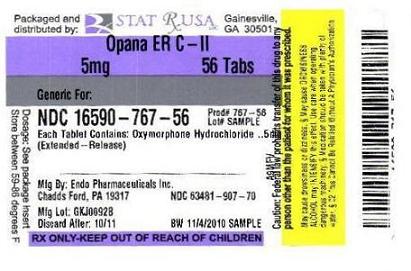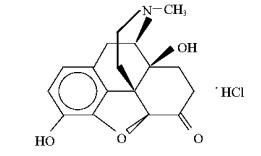 DRUG LABEL: OPANA
NDC: 16590-767 | Form: TABLET, FILM COATED, EXTENDED RELEASE
Manufacturer: STAT RX USA LLC
Category: prescription | Type: HUMAN PRESCRIPTION DRUG LABEL
Date: 20110715
DEA Schedule: CII

ACTIVE INGREDIENTS: OXYMORPHONE HYDROCHLORIDE 5 mg/1 1
INACTIVE INGREDIENTS: HYPROMELLOSES; METHYLPARABEN; PROPYLENE GLYCOL; SODIUM STEARYL FUMARATE; TITANIUM DIOXIDE; TRIACETIN; FD&C YELLOW NO. 6; FERROSOFERRIC OXIDE; CELLULOSE, MICROCRYSTALLINE; POLYETHYLENE GLYCOLS; POLYSORBATE 80; FERRIC OXIDE RED

WARNING:

OPANA ER contains oxymorphone, which is a morphine-like opioid agonist and a Schedule II controlled substance, with an abuse liability similar to other opioid analgesics.

Oxymorphone can be abused in a manner similar to other opioid agonists, legal or illicit. This should be considered when prescribing or dispensing OPANA ER in situations where the physician or pharmacist is concerned about an increased risk of misuse, abuse, or diversion.

OPANA ER is an extended-release oral formulation of oxymorphone indicated for the management of moderate to severe pain when a continuous, around-the-clock opioid analgesic is needed for an extended period of time.

OPANA ER is NOT intended for use as a prn analgesic.

OPANA ER Tablets are to be swallowed whole and are not to be broken, chewed, dissolved, or crushed. Taking broken, chewed, dissolved, or crushed OPANA ER Tablets leads to rapid release and absorption of a potentially fatal dose of oxymorphone.

Patients must not consume alcoholic beverages, or prescription or non-prescription medications containing alcohol, while on OPANA ER therapy. The co-ingestion of alcohol with OPANA ER may result in increased plasma levels and a potentially fatal overdose of oxymorphone.

DESCRIPTION

OPANA ER (oxymorphone hydrochloride) extended-release, is a semi-synthetic opioid analgesic supplied in 5 mg, 10 mg, 20 mg, and 40 mg tablet strengths for oral administration. The tablet strength describes the amount of oxymorphone hydrochloride per tablet. The tablets contain the following inactive ingredients: hypromellose, iron oxide black, methylparaben, propylene glycol, silicified microcrystalline cellulose, sodium stearyl fumarate, TIMERx® -N, titanium dioxide, and triacetin. The 5 mg, 10 mg and 20 mg tablets also contain macrogol, and polysorbate 80. In addition, the 5 mg tablets contain iron oxide red. The 10 mg tablets contain FD and C yellow No. 6. The 20 mg tablets contain FD and C blue No. 1, FD and C yellow No. 6, and D and C yellow No. 10. The 40 mg tablets contain FD and C yellow No. 6, D and C yellow No. 10, and lactose monohydrate.

Chemically, oxymorphone hydrochloride is 4, 5α -epoxy-3, 14-dihydroxy-17-methylmorphinan-6-one hydrochloride, a white or slightly off-white, odorless powder, which is sparingly soluble in alcohol and ether, but freely soluble in water. The molecular weight of oxymorphone hydrochloride is 337.80. The pKa1 and pKa2 of oxymorphone at 37°C are 8.17 and 9.54, respectively. The octanol/aqueous partition coefficient at 37°C and pH 7.4 is 0.98.

The structural formula for oxymorphone hydrochloride is as follows:

The tablet strengths, 5, 10, 20 and 40 mg, describe the amount of oxymorphone hydrochloride per tablet.

CLINICAL PHARMACOLOGY

Oxymorphone is an opioid agonist whose principal therapeutic action is analgesia. Other members of the class known as opioid agonists include substances such as morphine, oxycodone, hydromorphone, fentanyl, codeine, hydrocodone, and tramadol. In addition to analgesia, other pharmacological effects of opioid agonists include anxiolysis, euphoria, feelings of relaxation, respiratory depression, constipation, miosis, and cough suppression. Like all pure opioid agonist analgesics, with increasing doses there is increasing analgesia, unlike with mixed agonist/antagonists or non-opioid analgesics, where there is a limit to the analgesic effect with increasing doses. With pure opioid agonist analgesics, there is no defined maximum dose; the ceiling to analgesic effectiveness is imposed only by side effects, the more serious of which may include somnolence and respiratory depression.

Central Nervous System

The precise mechanism of the analgesic action is unknown. However, specific CNS (central nervous system) opioid receptors for endogenous compounds with opioid-like activity have been identified throughout the brain and spinal cord and play a role in the analgesic effects of this drug. In addition, opioid receptors have also been identified within the PNS (peripheral nervous system). The role that these receptors play in these drugs’ analgesic effects is unknown.

Opioids produce respiratory depression likely by direct action on brain stem respiratory centers. The respiratory depression involves a reduction in the responsiveness of the brain stem respiratory centers to both increases in carbon dioxide tension and electrical stimulation.

Opioids depress the cough reflex by direct effect on the cough center in the medulla oblongata. Antitussive effects may occur with doses lower than those usually required for analgesia. Opioids cause miosis, even in total darkness. Pinpoint pupils are a sign of opioid overdose but are not pathognomonic (e.g., pontine lesions of hemorrhagic or ischemic origin may produce similar findings). Marked mydriasis rather than miosis may be seen with hypoxia in overdose situations (see OVERDOSAGE: Signs and Symptoms).

Gastrointestinal Tract and Other Smooth Muscle

Opioids cause a reduction in motility associated with an increase in smooth muscle tone in the antrum of the stomach and duodenum. Digestion of food in the small intestine is delayed and propulsive contractions are decreased. Propulsive peristaltic waves in the colon are decreased, while tone may be increased to the point of spasm resulting in constipation. Other opioid-induced effects may include a reduction in gastric, biliary and pancreatic secretions, spasm of sphincter of Oddi, and transient elevations in serum amylase.

Cardiovascular System

Opioids produce peripheral vasodilation which may result in orthostatic hypotension. Release of histamine can occur and may contribute to opioid-induced hypotension. Manifestations of histamine release may include orthostatic hypotension, pruritus, flushing, red eyes, and sweating. Animal studies have shown that oxymorphone has a lower propensity to cause histamine release than other opioids.

Endocrine System

Opioids have been shown to have a variety of effects on the secretion of hormones. Opioids inhibit the secretion of ACTH, cortisol, and luteinizing hormone (LH) in humans. They also stimulate prolactin, growth hormone (GH) secretion, and pancreatic secretion of insulin and glucagon in humans and other species, rats and dogs. Thyroid stimulating hormone (TSH) has been shown to be both inhibited and stimulated by opioids.

Immune System

Opioids have been shown to have a variety of effects on components of the immune system in in vitro and animal models. The clinical significance of these findings is unknown.

Pharmacodynamics

Concentration-Efficacy Relationships

Studies in healthy volunteers reveal predictable relationships between OPANA ER dosage and plasma oxymorphone concentrations.

The minimum effective plasma concentration of oxymorphone for analgesia varies widely among patients, especially among patients who have been previously treated with agonist opioids. As a result, patients need to be individually titrated to achieve a balance between therapeutic and adverse effects. The minimum effective analgesic concentration of oxymorphone for any individual patient may increase over time due to an increase in pain, progression of disease, development of a new pain syndrome and/or potential development of analgesic tolerance.

Concentration-Adverse Experience Relationships

OPANA ER is associated with typical opioid-related adverse experiences. There is a general relationship between increasing opioid plasma concentration and increasing frequency of adverse experiences such as nausea, vomiting, CNS effects, and respiratory depression.

As with all opioids, the dose must be individualized (see DOSAGE AND ADMINISTRATION). The effective analgesic dose for some patients will be too high to be tolerated by other patients.

Pharmacokinetics

Absorption

The absolute oral bioavailability of oxymorphone is approximately 10%.

Steady-state levels are achieved after three days of multiple dose administration. Under both single-dose and steady-state conditions, dose proportionality has been established for the 5 mg, 10 mg, 20 mg, and 40 mg tablet strengths for both peak plasma levels (Cmax) and extent of absorption (AUC) (Table 1).

Table 1: Mean (+SD) OPANA ER Pharmacokinetic Parameters

Regimen | Dosage | Cmax (ng/mL) | AUC (ng·hr/mL) | T ½ (hr)
Single Dose | 5 mg 10 mg 20 mg 40 mg | 0.27±0.13 0.65±0.29 1.21±0.77 2.59±1.65 | 4.54±2.04 8.94±4.16 17.81±7.22 37.90±16.20 | 11.30±10.81 9.83±5.68 9.89±3.21 9.35±2.94
Multiple Dosea | 5 mg 10 mg 20 mg 40 mg | 0.70±0.55 1.24±0.56 2.54±1.35 4.47±1.91 | 5.60±3.87 9.77±3.52 19.28±8.32 36.98±13.53 | NA NA NA NA

NA = not applicable
a Results after 5 days of every 12 hours dosing.
Food Effect

Two studies examined the effect of food on the bioavailability of single doses of 20 and 40 mg of OPANA ER in healthy volunteers. In both studies, after the administration of OPANA ER, the Cmax was increased by approximately 50% in fed subjects compared to fasted subjects. A similar increase in Cmax was also observed with oxymorphone solution.

The AUC was unchanged in one study and increased by approximately 18% in the other study in fed subjects following the administration of OPANA ER. Examination of the AUC suggests that most of the difference between fed and fasting conditions occurs in the first four hours after dose administration. After oral dosing with a single dose of 40 mg, a peak oxymorphone plasma level of 2.8 ng/ml is achieved at 1 hour in fasted subjects and a peak of 4.25 ng/ml is achieved at 2 hours in fed subjects and that beyond the 12 hour time point, there is very little difference in the curves. As a result, OPANA ER should be dosed at least one hour prior to or two hours after eating (see DOSAGE AND ADMINISTRATION).

Ethanol Effect
In Vivo OPANA ER Formulation-Alcohol Interaction

Although in vitro studies have demonstrated that OPANA ER does not release oxymorphone more rapidly in 500 mL of 0.1N HCl solutions containing ethanol (4%, 20%, and 40%), there is an in vivo interaction with alcohol. An in vivo study examined the effect of alcohol (40%, 20%, 4% and 0%) on the bioavailability of a single dose of 40 mg of OPANA ER in healthy, fasted volunteers. The results showed that the oxymorphone mean AUC was 13% higher (not statistically significant) after co-administration of 240 mL of 40% alcohol. The AUC was essentially unaffected in subjects following the co-administration of OPANA ER and ethanol (240 mL of 20% or 4% ethanol).

There was a highly variable effect on Cmax with concomitant administration of alcohol and OPANA ER. The change in Cmax ranged from a decrease of 50% to an increase of 270% across all conditions studied. Following concomitant administration of 240 mL of 40% ethanol the Cmax increased on average by 70% and up to 270% in individual subjects. Following the concomitant administration of 240 mL of 20% ethanol, the Cmax increased on average by 31% and up to 260% in individual subjects. Following the concomitant administration of 240 mL of 4 % ethanol, the Cmax increased 7% on average and by as much as 110% for individual subjects. After oral dosing with a single dose of 40 mg in fasted subjects, the mean peak oxymorphone plasma level is 2.4 ng/mL and the median Tmax is 2 hours. Following co-administration of OPANA ER and alcohol (240 mL of 40% ethanol) in fasted subjects, the mean peak oxymorphone level is 3.9 ng/mL and the median Tmax is 1.5 hours (range 0.75 – 6 hours).

Co-administration of oxymorphone and ethanol must be avoided.

Oxymorphone may be expected to have additive effects when used in conjunction with alcohol, other opioids, or illicit drugs that cause central nervous system depression because respiratory depression, hypotension, and profound sedation, coma, or death may result.

Distribution

Formal studies on the distribution of oxymorphone in various tissues have not been conducted. Oxymorphone is not extensively bound to human plasma proteins; binding is in the range of 10% to 12%.

Metabolism

Oxymorphone is highly metabolized principally in the liver and undergoes reduction or conjugation with glucuronic acid to form both active and inactive metabolites. The two major metabolites of oxymorphone are oxymorphone-3-glucuronide and 6-OH-oxymorphone. The mean plasma AUC for oxymorphone-3-glucuronide is approximately 90-fold higher than the parent compound. The pharmacologic activity of the glucuronide metabolite has not been evaluated. 6-OH-oxymorphone has been shown in animal studies to have analgesic bioactivity. The mean plasma 6-OH-oymorphone AUC is approximately 70% of the oxymorphone AUC following single oral doses, but is essentially equivalent to the parent compound at steady-state.

Excretion

Because oxymorphone is extensively metabolized, less than 1% of the administered dose is excreted unchanged in the urine. On average, 33% to 38% of the administered dose is excreted in the urine as oxymorphone-3-glucuronide and 0.25% to 0.62% excreted as 6-OH-oxymorphone in subjects with normal hepatic and renal function. In animals given radiolabeled oxymorphone, approximately 90% of the administered radioactivity was recovered within 5 days of dosing. The majority of oxymorphone-derived radioactivity was found in the urine and feces.

Special Populations
Elderly

The steady-state plasma concentrations of oxymorphone, 6-OH-oxymorphone, and oxymorphone-3-glucuronide are approximately 40% higher in elderly subjects (≥ 65 years of age) than in young subjects (18 to 40 years of age). On average, age greater than 65 years was associated with a 1.4-fold increase in oxymorphone AUC and a 1.5-fold increase in Cmax. This observation does not appear related to a difference in body weight, metabolism, or excretion of oxymorphone (see PRECAUTIONS: Geriatric Use).

Gender

The effect of gender was evaluated following single- and multiple-doses of OPANA ER in male and female adult volunteers. There was a consistent tendency for female subjects to have slightly higher AUCss and Cmax values than male subjects; however, gender differences were not observed when AUCss and Cmax were adjusted by body weight.

Hepatic Impairment

The liver plays an important role in the pre-systemic clearance of orally administered oxymorphone. Accordingly, the bioavailability of orally administered oxymorphone may be markedly increased in patients with moderate to severe liver disease. The disposition of oxymorphone was compared in 6 patients with mild, 5 patients with moderate, and one patient with severe hepatic impairment and 12 subjects with normal hepatic function. The bioavailability of oxymorphone was increased by 1.6-fold in patients with mild hepatic impairment and by 3.7-fold in patients with moderate hepatic impairment. In one patient with severe hepatic impairment, the bioavailability was increased by 12.2-fold. The half-life of oxymorphone was not significantly affected by hepatic impairment (see DOSAGE AND ADMINISTRATION: Patients with Hepatic Impairment).

Renal Impairment

Data from a pharmacokinetic study involving 24 patients with renal dysfunction show an increase of 26%, 57%, and 65% in oxymorphone bioavailability in mild (creatinine clearance 51-80 mL/min; n=8), moderate (creatinine clearance 30-50 mL/min; n=8), and severe (creatinine clearance less than 30 mL/min; n=8) patients, respectively, compared to healthy controls.

Drug-Drug Interactions

In vitro studies revealed little to no biotransformation of oxymorphone to 6-OH-oxymorphone by any of the major cytochrome P450 (CYP P450) isoforms at therapeutically relevant oxymorphone plasma concentrations.

No inhibition of any of the major CYP P450 isoforms was observed when oxymorphone was incubated with human liver microsomes at concentrations of ≤ 50 μM. An inhibition of CYP3A4 activity occurred at oxymorphone concentrations ≥150 µM. Therefore, it is not expected that oxymorphone, or its metabolites will act as inhibitors of any of the major CYP P450 enzymes in vivo.

Increases in the activity of the CYP 2C9 and CYP 3A4 isoforms occurred when oxymorphone was incubated with human hepatocytes. However, clinical drug interaction studies with OPANA ER showed no induction of CYP450 3A4 or 2C9 enzyme activity, indicating that no dose adjustment for CYP 3A4- or 2C9-mediated drug-drug interactions is required.

CLINICAL TRIALS

The efficacy and safety of OPANA ER have been evaluated in double-blind, controlled clinical trials in opioid-naïve and opioid-experienced patients with moderate to severe pain including low back pain.

12-Week Study in Opioid-Naïve Patients with Low Back Pain

Patients with chronic low back pain who were suboptimally responsive to their current non-opioid therapy entered a 4-week, open-label dose titration phase. Patients initiated therapy with two days of treatment with OPANA ER 5 mg, every 12 hours. Thereafter, patients were titrated to a stabilized dose, at increments of 5-10 mg every 12 hours every 3-7 days. Of the patients who were able to stabilize within the Open-Label Titration Period, the mean±SD VAS score at Screening was 69.4±11.8 mm and at Baseline (beginning of Double-Blind Period) were 18.5±11.2 mm and 19.3±11.3 mm for the oxymorphone ER and placebo groups, respectively. Sixty three percent of the patients enrolled were able to titrate to a tolerable dose and were randomized into a 12-week double-blind treatment phase with placebo or their stabilized dose of OPANA ER. The mean±SD stabilized doses were 39.2±26.4 mg and 40.9±25.3 mg for the OPANA ER and placebo groups, respectively; total daily doses ranged from 10-140 mg. During the first 4 days of double-blind treatment patients were allowed an unlimited number of OPANA, an immediate-release (IR) formulation of oxymorphone, 5 mg tablets, every 4-6 hours as supplemental analgesia; thereafter the number of OPANA was limited to two tablets per day. This served as a tapering method to minimize opioid withdrawal symptoms in placebo patients. Sixty-eight percent of patients treated with OPANA ER completed the 12-week treatment compared to forty seven percent of patients treated with placebo. OPANA ER provided superior analgesia compared to placebo. The analgesic effect of OPANA ER was maintained throughout the double-blind treatment period in 89% of patients who completed the study. These patients reported a decrease, no change, or a ≤10 mm increase in VAS score from Day 7 until the end of the study.

A significantly higher proportion of OPANA ER patients (81.4%) had at least a 30% reduction in pain score from screening to study endpoint compared to placebo patients (51.7%). The proportion of patients with various degrees of improvement from screening to study endpoint is shown in Figure 1.

Figure 1: Percent Reduction in Average Pain Intensity from Screening to Final Visit

12-Week Study in Opioid-Experienced Patients with Low Back Pain

Patients currently on chronic opioid therapy entered a 4-week, open-label titration phase with OPANA ER dosed every 12 hours at an approximated equianalgesic dose of their pre-study opioid medication. Of the patients who were able to stabilize within the Open‑Label Titration Period, the mean±SD VAS score at Screening was 69.5±17.0 mm and at Baseline (beginning of Double-Blind Period) were 23.9±12.1 mm and 22.2±10.8 mm for the oxymorphone ER and placebo groups, respectively. Stabilized patients entered a 12‑week double-blind treatment phase with placebo or their stabilized dose of OPANA ER. The mean±SD stabilized doses were 80.9±59.3 mg and 93.3±61.3 mg for the OPANA ER and placebo groups, respectively; total daily doses ranged from 20-260 mg. During the first 4 days of double-blind treatment, patients were allowed an unlimited number of OPANA 5 mg tablets, every 4-6 hours as supplemental analgesia; thereafter the number of OPANA was limited to two tablets per day. This served as a tapering method to minimize opioid withdrawal symptoms in placebo patients. Fifty seven percent of patients were titrated to a stabilized dose within approximately 4 weeks of OPANA ER dose titration. Seventy percent of patients treated with OPANA ER and 26% of patients treated with placebo completed the 12-week treatment. OPANA ER provided superior analgesia compared to placebo . The analgesic effect of OPANA ER was maintained throughout the double-blind treatment period in 80 % of patients who completed the study. These patients reported a decrease, no change, or a ≤10 mm increase in VAS score from Day 7 until the end of the study.

A significantly higher proportion of OPANA ER patients (79.7%) had at least a 30% reduction in pain score from screening to study endpoint compared to placebo patients (34.8%). Proportion of patients with various degrees of improvement from screening to study endpoint is shown in Figure 2.

Figure 2: Percent Reduction in Average Pain Intensity from Screening to Final Visit

INDICATIONS AND USAGE

OPANA ER is indicated for the relief of moderate to severe pain in patients requiring continuous, around-the-clock opioid treatment for an extended period of time.

OPANA ER is not intended for use as a prn analgesic.

OPANA ER is not indicated for pain in the immediate post-operative period (12-24 hours following surgery) for patients not previously taking opioids because of the risk of oversedation and respiratory depression requiring reversal with opioid antagonists.

OPANA ER is not indicated for pain in the post-operative period if the pain is mild or not expected to persist for an extended period of time.

CONTRAINDICATIONS

OPANA ER is contraindicated in patients with a known hypersensitivity to oxymorphone hydrochloride or to any of the other ingredients in OPANA ER, or with known hypersensitivity to morphine analogs such as codeine.

OPANA ER is not indicated for pain in the immediate post-operative period (the first 12-24 hours following surgery), or if the pain is mild, or not expected to persist for an extended period of time. OPANA ER is only indicated for post-operative use if the patient is already receiving the drug prior to surgery or if the post-operative pain is expected to be moderate or severe and persist for an extended period of time. Physicians should individualize treatment, moving from parenteral to oral analgesics as appropriate. (See American Pain Society guidelines).

OPANA ER is contraindicated in any situation where opioids are contraindicated such as: patients with respiratory depression (in the absence of resuscitative equipment or in unmonitored settings), and in patients with acute or severe bronchial asthma or hypercarbia.

OPANA ER, like all opioids, is contraindicated in any patient who has or is suspected of having paralytic ileus.

OPANA ER is contraindicated in patients with moderate and severe hepatic impairment (see CLINICAL PHARMACOLOGY, PRECAUTIONS and DOSAGE AND ADMINISTRATION).

WARNINGS

OPANA ER TABLETS are to be swallowed whole, and are not to be broken, chewed, crushed or dissolved. Taking broken, chewed, crushed or dissolved OPANA ER TABLETS could lead to the rapid release and absorption of a potentially fatal dose of oxymorphone.

Patients must not consume alcoholic beverages, or prescription or non-prescription medications containing alcohol, while on OPANA ER therapy. The co-ingestion of alcohol with OPANA ER may result in increased plasma levels and a potentially fatal overdose of oxymorphone.

Misuse, Abuse and Diversion of Opioids

OPANA ER contains oxymorphone, an opioid agonist similar to morphine, and is a Schedule II controlled substance. Opioid agonists have the potential for being abused and are sought by drug abusers and people with addiction disorders and are subject to criminal diversion.

Oxymorphone can be abused in a manner similar to other opioid agonists, legal or illicit. This should be considered when prescribing or dispensing OPANA ER in situations where the physician or pharmacist is concerned about an increased risk of misuse, abuse, or diversion.

OPANA ER tablets may be abused by crushing, chewing, snorting or injecting the product. These practices will result in the uncontrolled delivery of the opioid and pose a significant risk to the abuser that could result in overdose and death (see WARNINGS and WARNINGS: Drug Abuse and Addiction).

Concerns about abuse, addiction, and diversion should not prevent the proper management of pain.

Healthcare professionals should contact their State Professional Licensing Board, or State Controlled Substances Authority for information on how to prevent and detect abuse or diversion of this product.

Interactions with Alcohol and Drugs of Abuse

Oxymorphone may be expected to have additive effects when used in conjunction with alcohol, other opioids, or illicit drugs that cause central nervous system depression because respiratory depression, hypotension, and profound sedation or coma may result. An in vivo study examined the effect of alcohol (40%, 20%, 4% and 0%) on the bioavailability of a single dose of 40 mg of OPANA ER in healthy, fasted volunteers. The results showed that the oxymorphone mean AUC was 13% higher (not statistically significant) after co-administration of 240 mL of 40% alcohol. The AUC was essentially unaffected in subjects following the co-administration of OPANA ER and ethanol (240 mL of 20% or 4% ethanol).

There was a highly variable effect on Cmax with concomitant administration of alcohol and OPANA ER. The change in Cmax ranged from a decrease of 50% to an increase of 270% across all conditions studied. Following concomitant administration of 240 mL of 40% ethanol the Cmax increased on average by 70%, and up to 270% in individual subjects. Following the concomitant administration of 240mL of 20% ethanol the Cmax increased on average by 31% and up to 260% in individual subjects. Following the concomitant administration of 240 mL of 4 % ethanol, the Cmax increased by 7% on average and as much as 110% for individual subjects.

Drug Abuse and Addiction
Controlled Substance

OPANA ER contains oxymorphone, an opioid with an abuse liability similar to morphine and other opioid agonists and is a Schedule II controlled substance. OPANA ER and other opioids used in analgesia, can be abused and are subject to criminal diversion (see WARNINGS: Misuse, Abuse and Diversion of Opioids).

Drug addiction is characterized by a preoccupation with the procurement, hoarding, and abuse of drugs for non-medicinal purposes. Drug addiction is treatable, utilizing a multi-disciplinary approach, but relapse is common.

"Drug seeking" behavior is very common to addicts and drug abusers. Drug-seeking tactics include emergency calls or visits near the end of office hours, refusal to undergo appropriate examination, testing or referral, repeated claims of loss of prescriptions, tampering with prescriptions and reluctance to provide prior medical records or contact information for other treating physician(s). “Doctor shopping” (visiting multiple prescribers) to obtain additional prescriptions is common among drug abusers and people suffering from untreated addiction. Preoccupation with achieving adequate pain relief can be appropriate behavior in a patient with poor pain control.

Abuse and addiction are separate and distinct from physical dependence and tolerance. Physicians should be aware that addiction may not be accompanied by concurrent tolerance and symptoms of physical dependence in all addicts. In addition, abuse of opioids can occur in the absence of true addiction and is characterized by misuse for non-medical purposes, often in combination with other psychoactive substances. OPANA ER, like other opioids, may be diverted for non-medical use. Careful record-keeping of prescribing information, including quantity, frequency, and renewal requests is strongly advised.

Abuse of OPANA ER poses a risk of overdose and death. This risk is increased with concurrent abuse of OPANA ER with alcohol and other substances. In addition, parenteral drug abuse is commonly associated with transmission of infectious disease such as hepatitis and HIV.

Proper assessment of the patient, proper prescribing practices, periodic re-evaluation of therapy, and proper dispensing and storage are appropriate measures that help to limit abuse of opioid drugs.

Infants born to mothers physically dependent on opioids will also be physically dependent and may exhibit respiratory difficulties and withdrawal symptoms (see PRECAUTIONS: Usage in Pregnancy and PRECAUTIONS: Labor and Delivery).

Respiratory Depression

Respiratory depression is the chief hazard of OPANA ER. Respiratory depression is a particular potential problem in elderly or debilitated patients as well as in those suffering from conditions accompanied by hypoxia or hypercapnia when even moderate therapeutic doses may dangerously decrease pulmonary ventilation.

OPANA ER should be administered with extreme caution to patients with conditions accompanied by hypoxia, hypercapnia, or decreased respiratory reserve such as: asthma, chronic obstructive pulmonary disease or cor pulmonale, severe obesity, sleep apnea syndrome, myxedema, kyphoscoliosis, CNS depression or coma. In these patients, even usual therapeutic doses of oxymorphone may decrease respiratory drive while simultaneously increasing airway resistance to the point of apnea. Alternative non-opioid analgesics should be considered, and oxymorphone should be employed only under careful medical supervision at the lowest effective dose in such patients.

Interactions with Other Central Nervous System Depressants

Patients receiving other opioid analgesics, general anesthetics, phenothiazines or other tranquilizers, sedatives, hypnotics, or other CNS depressants (including alcohol) concomitantly with oxymorphone may experience respiratory depression, hypotension, profound sedation, or coma (see PRECAUTIONS: Drug-Drug Interactions).

Head Injury and Increased Intracranial Pressure

In the presence of head injury, intracranial lesions or a preexisting increase in intracranial pressure, the possible respiratory depressant effects of opioid analgesics and their potential to elevate cerebrospinal fluid pressure (resulting from vasodilation following CO2 retention) may be markedly exaggerated. Furthermore, opioid analgesics can produce effects on pupillary response and consciousness, which may obscure neurologic signs of further increases in intracranial pressure in patients with head injuries.

Hypotensive Effect

OPANA ER, like all opioid analgesics, may cause severe hypotension in an individual whose ability to maintain blood pressure has been compromised by a depleted blood volume, or after concurrent administration with drugs such as phenothiazines or other agents which compromise vasomotor tone. OPANA ER, like all opioid analgesics, should be administered with caution to patients in circulatory shock, since vasodilation produced by the drug may further reduce cardiac output and blood pressure.

Hepatic Impairment

A study of OPANA ER in patients with hepatic disease indicated greater plasma concentrations than those with normal hepatic function (see CLINICAL PHARMACOLOGY). OPANA ER should be used with caution in patients with mild impairment. These patients should be started with the lowest dose and titrated slowly while carefully monitoring for side effects. OPANA ER is contraindicated for patients with moderate and severe hepatic impairment (see CONTRAINDICATIONS, WARNINGS, and DOSAGE AND ADMINISTRATION).

PRECAUTIONS

General

Opioid analgesics should be used with caution especially when combined with other drugs, and should be reserved for cases where the benefits of opioid analgesia outweigh the known potential risks of respiratory depression, altered mental state and postural hypotension. OPANA ER should be used with caution in elderly and debilitated patients and in patients who are known to be sensitive to central nervous system depressants, such as those with cardiovascular, pulmonary, renal, or hepatic disease.

OPANA ER should be used with caution in the following conditions: acute alcoholism; adrenocortical insufficiency (e.g., Addison's disease); CNS depression or coma; delirium tremens; kyphoscoliosis associated with respiratory depression; myxedema or hypothyroidism; prostatic hypertrophy or urethral stricture; severe impairment of pulmonary or renal function; moderate impairment of hepatic function; and toxic psychosis.

The administration of oxymorphone may obscure the diagnosis or clinical course in patients with acute abdominal conditions. Oxymorphone may aggravate convulsions in patients with convulsive disorders, and all opioids may induce or aggravate seizures in some clinical settings.

OPANA ER is intended for use in patients who require more than several days continuous treatment with an opioid analgesic.

Ambulatory Surgery and Post-Operative Use

OPANA ER is not indicated for pre-emptive analgesia (administration pre-operatively for the management of post-operative pain).

OPANA ER is not indicated for pain in the immediate post-operative period (12-24 hours following surgery) for patients not previously taking opioids because of the risk of oversedation and respiratory depression requiring reversal with opioid antagonists.

OPANA ER is not indicated for pain in the post-operative period if the pain is mild or not expected to persist for an extended period of time.

OPANA ER is only indicated for postoperative use in the patient if the patient is already receiving the drug prior to surgery or if the postoperative pain is expected to be moderate to severe and persist for an extended period of time. Physicians should individualize treatment, moving from parenteral to oral analgesics as appropriate (see American Pain Society guidelines).

Patients who are already receiving OPANA ER as part of ongoing analgesic therapy may be safely continued on the drug if appropriate dosage adjustments are made considering the procedure, other drugs given, and the temporary changes in physiology caused by the surgical intervention (see DOSAGE AND ADMINISTRATION).

OPANA ER, like other opioids, decreases bowel motility. Ileus is a common post-operative complication, especially after intra-abdominal surgery with opioid analgesia. Caution should be taken to monitor for decreased bowel motility in post-operative patients receiving opioids. Standard supportive therapy should be implemented.

Use in Pancreatic/Biliary Tract Disease

OPANA ER, like other opioids, may cause spasm of the sphincter of Oddi and should be used with caution in patients with biliary tract disease, including acute pancreatitis.

Physical Dependence and Tolerance

Physical dependence is the occurrence of withdrawal symptoms after abrupt discontinuation of a drug or upon administration of an opioid antagonist or mixed opioid agonist/antagonist agent. Tolerance is the need for increasing doses of opioids to maintain a defined effect such as analgesia (in the absence of disease progression or other external factors). The development of physical dependence and tolerance is not unusual during chronic opioid therapy.

If OPANA ER is abruptly discontinued in a physically-dependent patient, an abstinence syndrome may occur. Some or all of the following can characterize this syndrome: restlessness, lacrimation, rhinorrhea, yawning, perspiration, chills, myalgia, and mydriasis. Other symptoms also may develop, including: irritability, anxiety, backache, joint pain, weakness, abdominal cramps, insomnia, nausea, anorexia, vomiting, diarrhea, or increased blood pressure, respiratory rate, or heart rate.

In general, OPANA ER should not be abruptly discontinued. However, OPANA ER, like other opioids, can be safely discontinued without the development of withdrawal symptoms by slowly tapering the daily dose (see DOSAGE AND ADMINISTRATION: Cessation of Therapy).

Information for Patients/Caregivers

1. Patients should be advised that OPANA ER contains oxymorphone, a morphine-like pain reliever, and should be taken only as directed.
2. Patients should be advised that OPANA ER is designed to work properly only if swallowed whole. The extended-release tablets may release all their contents at once if broken, chewed or crushed, resulting in a risk of fatal overdose of oxymorphone.
3. Patients must not consume alcoholic beverages, or prescription or non-prescription medications containing alcohol, while on OPANA ER therapy. The co-ingestion of alcohol with OPANA ER may result in increased plasma levels and a potentially fatal overdose of oxymorphone.
4. Appropriate pain management requires changes in the dose to maintain best pain control. Patients should be advised of the need to contact their physician if pain control is inadequate, but not to change the dose of OPANA ER without consulting their physician.
5. Patients should be advised to report episodes of breakthrough pain and adverse experiences occurring during therapy to their doctor. Individualization of dosage is essential to make optimal use of this medication.
6. Patients should be cautioned that OPANA ER may cause drowsiness, dizziness, or lightheadedness, and may impair mental and/or physical abilities required for the performance of potentially hazardous tasks, such as driving a car, operating machinery, etc.
7. Patients should not combine OPANA ER with alcohol or other central nervous system depressants (sleep aids, tranquilizers) except by the orders of the prescribing physician, because additive effects may occur, resulting in serious injury or death.
8. Patients taking OPANA ER should be advised of the potential for severe constipation. Appropriate laxatives and/or stool softeners and other therapeutic approaches may be considered for use with the initiation of OPANA ER therapy.
9. Patients should be advised not to adjust the dose of OPANA ER without consulting the prescribing professional.
10. Patients should be advised that OPANA ER is a potential drug of abuse. They should protect it from theft, and it should never be given to anyone other than the individual for whom it was prescribed.
11. Women of childbearing potential who become, or are planning to become pregnant should be advised to consult their physician regarding the effects of opioid analgesics and other drug use during pregnancy on themselves and their unborn child.
12. If patients have been receiving treatment with OPANA ER for more than a few days to weeks and cessation of therapy is indicated, they should be counseled on the importance of safely tapering the dose and that abruptly discontinuing the medication could precipitate withdrawal symptoms. The physician should determine a dose schedule to accomplish a gradual discontinuation of the medication.
13. As with any potent opioid, misuse of OPANA ER may result in serious adverse events. Patients should be instructed to keep OPANA ER in a secure place out of the reach of children and pets. Accidental consumption especially in children can result in overdose or death. When OPANA ER is no longer needed, the unused tablets should be destroyed by flushing down the toilet.

Use in Drug and Alcohol Addiction

OPANA ER is not approved for use in detoxification or maintenance treatment of opioid addiction. However, the history of an addictive disorder does not necessarily preclude the use of this medication for the treatment of chronic pain. These patients will require intensive monitoring for signs of misuse, abuse, or addiction.

Drug-Drug Interactions

Oxymorphone is highly metabolized principally in the liver and undergoes reduction or conjugation with glucuronic acid to form both active and inactive metabolites (see Pharmacokinetics: Metabolism).

Use with CNS Depressants

The concomitant use of other CNS depressants including sedatives, hypnotics, tranquilizers, general anesthetics, phenothiazines, other opioids, and alcohol may produce additive CNS depressant effects. OPANA ER, like all opioid analgesics, should be started at 1/3 to 1/2 of the usual dose in patients who are concurrently receiving other central nervous system depressants including sedatives or hypnotics, general anesthetics, phenothiazines, tranquilizers, and alcohol because respiratory depression, hypotension, and profound sedation or coma may result, and titrated slowly as necessary for adequate pain relief.

Additive effects resulting in respiratory depression, hypotension, profound sedation or coma may result if these drugs are taken in combination with the usual doses of OPANA ER. No specific interaction between oxymorphone and monoamine oxidase inhibitors has been observed, but caution in the use of any opioid in patients taking this class of drugs is appropriate.

When combined therapy with any of the above medications is contemplated, the dose of one or both agents should be reduced (see WARNINGS and DOSAGE AND ADMINISTRATION).

Interactions with Mixed Agonist/Antagonist Opioid Analgesics

Agonist/antagonist analgesics (i.e., pentazocine, nalbuphine, butorphanol, or buprenorphine) should not be administered to patients who have received or are receiving a course of therapy with a pure opioid agonist analgesic, such as OPANA ER. In this situation, mixed agonist/antagonist analgesics may reduce the analgesic effect of OPANA ER and/or may precipitate withdrawal symptoms.

Other

Anticholinergics or other medications with anticholinergic activity when used concurrently with opioid analgesics may result in increased risk of urinary retention and/or severe constipation, which may lead to paralytic ileus.

In addition, CNS side effects have been reported (confusion, disorientation, respiratory depression, apnea, seizures) following coadministration of cimetidine with opioid analgesics; no clear-cut cause and effect relationship was established.

Carcinogenesis, Mutagenesis, Impairment of Fertility

Carcinogenesis: Long-term studies have been completed to evaluate the carcinogenic potential of oxymorphone in both Sprague-Dawley rats and CD-1 mice. Oxymorphone HCl was administered to Sprague-Dawley rats (2.5, 5, and 10 mg/kg/day in males and 5, 10, and 25 mg/kg/day in females) for 2 years by oral gavage. The systemic drug exposure (AUC ng•h/mL) at the 10 mg/kg/day in male rats was 0.34-fold and at the 25 mg/kg/day dose in female rats was 1.5-fold the human exposure at a dose of 260 mg/day. No evidence of carcinogenic potential was observed in rats. Oxymorphone HCl was administered to CD-1 mice (10, 25, 75 and 150 mg/kg/day) for 2 years by oral gavage. The systemic drug exposure (AUC ng•h/mL) at the 150 mg/kg/day dose in mice was 14.5-fold (in males) and 17.3-fold (in females) times the human exposure at a dose of 260 mg/day. No evidence of carcinogenic potential was observed in mice.

Mutagenesis: Oxymorphone hydrochloride was not mutagenic when tested in the in vitro bacterial reverse mutation assay (Ames test) at concentrations of ≤5270 µg/plate, or in an in vitro mammalian cell chromosome aberration assay performed with human peripheral blood lymphocytes at concentrations ≤5000 µg/ml with or without metabolic activation. Oxymorphone hydrochloride tested positive in both the rat and mouse in vivo micronucleus assays. An increase in micronucleated polychromatic erythrocytes occurred in mice given doses ≥250 mg/kg and in rats given doses of 20 and 40 mg/kg. A subsequent study demonstrated that oxymorphone hydrochloride was not aneugenic in mice following administration of up to 500 mg/kg. Additional studies indicate that the increased incidence of micronucleated polychromatic erythrocytes in rats may be secondary to increased body temperature following oxymorphone administration. Doses associated with increased micronucleated polychromatic erythrocytes also produce a marked, rapid increase in body temperature. Pretreatment of animals with sodium salicylate minimized the increase in body temperature and prevented the increase in micronucleated polychromatic erythrocytes after administration of 40 mg/kg oxymorphone.

Impairment of fertility: Oxymorphone hydrochloride did not affect reproductive function or sperm parameters in male rats at any dose tested (≤50 mg/kg/day). In female rats, an increase in the length of the estrus cycle and decrease in the mean number of viable embryos, implantation sites and corpora lutea were observed at doses of oxymorphone ≥10 mg/kg/day. The dose of oxymorphone associated with reproductive findings in female rats is 1.2-fold the human dose of 40 mg every 12 hours based on a body surface area. The dose of oxymorphone that produced no adverse effects on reproductive findings in female rats is 0.6-fold the human dose of 40 mg every 12 hours on a body surface area basis.

Pregnancy

The safety of using oxymorphone in pregnancy has not been established with regard to possible adverse effects on fetal development. The use of OPANA ER in pregnancy, in nursing mothers, or in women of child-bearing potential requires that the possible benefits of the drug be weighed against the possible hazards to the mother and the child (see PRECAUTIONS).

Teratogenic Effects
Pregnancy Category C

Oxymorphone hydrochloride administration did not cause malformations at any doses evaluated during developmental toxicity studies in rats (≤25 mg/kg/day) or rabbits (≤50 mg/kg/day). These doses are ~3-fold and ~12-fold the human dose of 40 mg every 12 hours, based on body surface area. There were no developmental effects in rats treated with 5 mg/kg/day or rabbits treated with 25 mg/kg/day. Fetal weights were reduced in rats and rabbits given doses of ≥10 mg/kg/day and 50 mg/kg/day, respectively. These doses are ~1.2-fold and ~6-fold the human dose of 40 mg every 12 hours based on body surface area, respectively. There were no effects of oxymorphone hydrochloride on intrauterine survival in rats at doses ≤25 mg/kg/day, or rabbits at ≤50 mg/kg/day in these studies (see Non-teratogenic Effects, below). In a study that was conducted prior to the establishment of Good Laboratory Practices (GLP) and not according to current recommended methodology, a single subcutaneous injection of oxymorphone hydrochloride on gestation day 8 was reported to produce malformations in offspring of hamsters that received 15.5-fold the human dose of 40 mg every 12 hours based on body surface area. This dose also produced 83% maternal lethality.

There are no adequate and well-controlled studies in pregnant women. OPANA ER should be used during pregnancy only if the potential benefit justifies the potential risk to the fetus.

Non-teratogenic Effects

Oxymorphone hydrochloride administration to female rats during gestation in a pre- and postnatal developmental toxicity study reduced mean litter size (18%) at a dose of 25 mg/kg/day, attributed to an increased incidence of stillborn pups. An increase in neonatal death occurred at ≥5 mg/kg/day. Post-natal survival of the pups was reduced throughout weaning following treatment of the dams with 25 mg/kg/day. Low pup birth weight and decreased postnatal weight gain occurred in pups born to oxymorphone-treated female rats given a dose of 25 mg/kg/day. This dose is ~3-fold higher than the human dose of 40 mg every 12 hours on a body surface area basis.

Prolonged use of opioid analgesics during pregnancy may cause fetal-neonatal physical dependence. Neonatal withdrawal may occur. Symptoms usually appear during the first days of life and may include convulsions, irritability, excessive crying, tremors, hyperactive reflexes, fever, vomiting, diarrhea, sneezing, yawning, and increased respiratory rate.

Labor and Delivery

Opioids cross the placenta and may produce respiratory depression and psycho-physiologic effects in neonates. OPANA ER is not recommended for use in women during and immediately prior to labor, when use of shorter acting analgesics or other analgesic techniques are more appropriate. Occasionally, opioid analgesics may prolong labor through actions which temporarily reduce the strength, duration and frequency of uterine contractions. However this effect is not consistent and may be offset by an increased rate of cervical dilatation, which tends to shorten labor. Neonates whose mothers received opioid analgesics during labor should be observed closely for signs of respiratory depression. A specific opioid antagonist, such as naloxone or nalmefene, should be available for reversal of opioid-induced respiratory depression in the neonate.

Nursing Mothers

It is not known whether oxymorphone is excreted in human milk. Because many drugs, including some opioids, are excreted in human milk, caution should be exercised when OPANA ER is administered to a nursing woman. Ordinarily, nursing should not be undertaken while a patient is receiving oxymorphone because of the possibility of sedation and/or respiratory depression in the infant.

Pediatric Use

Safety and effectiveness of OPANA ER in pediatric patients below the age of 18 years have not been established.

Geriatric Use

OPANA ER should be used with caution in elderly patients. The plasma levels of oxymorphone are about 40% higher in elderly (≥65 years of age) than in younger subjects (see CLINICAL PHARMACOLOGY). Elderly patients should initially receive smaller starting doses of oxymorphone and dose titration should proceed cautiously.

Of the total number of subjects in clinical studies of OPANA ER, 27 percent were 65 and over, while 9 percent were 75 and over. No overall differences in effectiveness were observed between these subjects and younger subjects. There were several adverse events that were more frequently observed in subjects 65 and over compared to younger subjects. These adverse events included dizziness, somnolence, confusion, and nausea.

Hepatic Impairment

A study of OPANA ER in patients with hepatic disease indicated greater plasma concentrations than those with normal hepatic function (see CLINICAL PHARMACOLOGY). OPANA ER should be used with caution in patients with mild impairment. These patients should be started with the lowest dose and titrated slowly while carefully monitoring for side effects. OPANA ER is contraindicated for patients with moderate and severe hepatic impairment (see CONTRAINDICATIONS, WARNINGS, and DOSAGE AND ADMINISTRATION).

Renal Impairment

In a study of OPANA ER, patients with moderate to severe renal impairment were shown to have an increase in bioavailability ranging from 57-65% (see CLINICAL PHARMACOLOGY). These patients should be started cautiously with lower doses of OPANA ER and titrated slowly while carefully monitored for side effects (see DOSAGE AND ADMINISTRATION).

Gender Differences

When normalized for body weight, gender differences were not observed (see CLINICAL PHARMACOLOGY). In clinical studies, the overall incidence rates for one or more adverse events were slightly higher among females than males for both OPANA ER subjects and placebo subjects.

ADVERSE REACTIONS

Tables 2 and 3 list the most frequently occurring adverse reactions (in at least 5% of patients) from the placebo-controlled trials in patients with low back pain.

Table 2: Treatment-Emergent Adverse Events Reported in ≥5% of Patients During the Open-Label Titration Period and Double-Blind Treatment Period by Preferred Term —Number (%) of Treated Patients (12-Week Study In Opioid-Naïve Patients with Low Back Pain)
 | Open-Label Titration Period | Double-Blind Treatment Period
 | OPANA ER | OPANA ER | Placebo
Preferred Term | (N = 325) | (N = 105) | (N = 100)
Constipation | 26.2% | 6.7% | 1.0%
Somnolence | 19.1% | 1.9% | 0%
Nausea | 18.2% | 11.4% | 9.0%
Dizziness | 11.1% | 4.8% | 3.0%
Headache | 10.5% | 3.8% | 2.0%
Pruritus | 6.8% | 2.9% | 1.0%

Table 3. Treatment-Emergent Adverse Events Reported in ≥5% of Patients During the Open-Label Titration Period and Double-Blind Treatment Period by Preferred Term —Number (%) of Treated Patients (12-Week Study In Opioid-Experienced Patients with Low Back Pain)
 | Open-Label Titration Period | Double-Blind Treatment Period
 | OPANA ER | OPANA ER | Placebo
Preferred Term | (N = 250) | (N = 70) | (N = 72)
Nausea | 19.6% | 2.9% | 1.4%
Constipation | 11.6% | 5.7% | 1.4%
Headache | 11.6% | 2.9% | 0%
Somnolence | 11.2% | 2.9% | 0%
Vomiting | 8.8% | 0% | 1.4%
Pruritus | 7.6% | 0% | 0%
Dizziness | 6.4% | 0% | 0%

Adverse Reactions Reported in Placebo-Controlled Trials

The following table lists adverse reactions that were reported in at least 2% of patients in placebo-controlled trials (N=5)

Table 4: Adverse Reactions Reported in Placebo-Controlled Clinical Trials with Incidence ≥2% in Patients Receiving OPANA ER.
MedDRA Preferred Term | OPANA ER (N=1259) | Placebo (N=461)
Nausea | 33.1% | 13.2%
Constipation | 27.6% | 13.2%
Dizziness (Exc Vertigo) | 17.8% | 7.6%
Somnolence | 17.2% | 2.2%
Vomiting | 15.6% | 4.1%
Pruritus | 15.2% | 7.6%
Headache | 12.2% | 5.6%
Sweating increased | 8.6% | 8.7%
Dry mouth | 6.4% | 0.7%
Sedation | 5.9% | 7.6%
Diarrhea | 4.3% | 5.6%
Insomnia | 4.0% | 2.0%
Fatigue | 3.9% | 1.3%
Appetite decreased | 2.9% | 0.4%
Abdominal pain | 2.5% | 1.5%

Adverse Reactions Reported in All Clinical Trials

A total of 2011 patients were treated with OPANA ER in the Phase 2/3 controlled and open-label clinical trials. The clinical trials consisted of patients with moderate to severe chronic pain and post surgical pain.

The adverse reactions are presented in the following manner: most common, common, and less common adverse reactions.

The most common adverse drug reactions (≥10%) reported at least once by patients treated with OPANA ER in the clinical trials were nausea, constipation, dizziness (exc. vertigo), vomiting, pruritus, somnolence, headache, sweating increased, and sedation.

The common (≥1% - less than 10%) adverse drug reactions reported at least once by patients treated with OPANA ER in the clinical trials organized by MedDRA’s (Medical Dictionary for Regulatory Activities) System Organ Class were:

Eye disorders: vision blurred

Gastrointestinal disorders: diarrhea, abdominal pain, dyspepsia

General disorders and administration site conditions: dry mouth, appetite decreased, fatigue, lethargy, weakness, pyrexia, dehydration, weight decreased, edema

Nervous system disorders: insomnia

Psychiatricdisorders: anxiety, confusion, disorientation, restlessness, nervousness, depression

Respiratory, thoracic and mediastinal disorders: dyspnea

Vascular disorders: flushing and hypertension

Other less common adverse reactions known with opioid treatment that were seen less than 1% in the OPANA ER trials include the following in alphabetical order.

Abdominal distention, agitation, allergic reactions, bradycardia, central nervous system depression, clamminess, depressed level of consciousness, dermatitis, difficult micturition, dysphoria, euphoric mood, feeling jittery, hallucination, hot flashes, hypersensitivity, hypotension, hypoxia, ileus, mental impairment, mental status changes, miosis, oxygen saturation decreased, palpitation, postural hypotension, respiratory depression, respiratory distress, respiratory rate decreased, syncope, tachycardia, urinary retention, urticaria, and visual disturbances.

OVERDOSAGE

Signs and Symptoms

Acute overdosage with OPANA ER is characterized by respiratory depression (a decrease in respiratory rate and/or tidal volume, Cheyne-Stokes respiration, cyanosis), extreme somnolence progressing to stupor or coma, skeletal muscle flaccidity, cold and clammy skin, constricted pupils and sometimes bradycardia and hypotension. In severe overdosage, apnea, circulatory collapse, cardiac arrest and death may occur.

OPANA ER may cause miosis, even in total darkness. Pinpoint pupils are a sign of opioid overdose but are not pathognomonic (e.g., pontine lesions of hemorrhagic or ischemic origin may produce similar findings). Marked mydriasis rather than miosis may be seen with hypoxia in overdose situations (see CLINICAL PHARMACOLOGY: Central Nervous System).

Treatment

In the treatment of OPANA ER overdosage, primary attention should be given to the re-establishment of a patent airway and institution of assisted or controlled ventilation. Supportive measures (including oxygen and vasopressors) should be employed in the management of circulatory shock and pulmonary edema accompanying overdose as indicated. Cardiac arrest or arrhythmias may require cardiac massage or defibrillation. Elimination or evacuation of gastric contents may be necessary in order to eliminate unabsorbed drug. Before attempting treatment by gastric emptying or activated charcoal, care should be taken to secure the airway.

The opioid antagonist naloxone hydrochloride is a specific antidote against respiratory depression, which may result from overdosage or unusual sensitivity to opioids including OPANA ER. Therefore, an appropriate dose of naloxone hydrochloride should be administered (usual initial adult dose 0.4 mg-2 mg) preferably by the intravenous route and simultaneously with efforts at respiratory resuscitation. Nalmefene is an alternative pure opioid antagonist, which may be administered as a specific antidote to respiratory depression resulting from opioid overdose. Since the duration of action of OPANA ER may exceed that of the antagonist, the patient should be kept under continued surveillance and repeated doses of the antagonist should be administered according to the antagonist labeling as needed to maintain adequate respiration.

In patients receiving OPANA ER, opioid antagonists should not be administered in the absence of clinically significant respiratory or circulatory depression secondary to OPANA ER overdose. They should be administered cautiously to persons who are known, or suspected to be, physically dependent on any opioid agonist including OPANA ER. In such cases, an abrupt or complete reversal of opioid effects may precipitate an acute abstinence syndrome. In an individual physically dependent on opioids, administration of the usual dose of the antagonist will precipitate an acute withdrawal syndrome. The severity of the withdrawal syndrome produced will depend on the degree of physical dependence and the dose of the antagonist administered. If respiratory depression is associated with muscular rigidity, administration of a neuromuscular blocking agent may be necessary to facilitate assisted or controlled ventilation. Muscular rigidity may also respond to opioid antagonist therapy

DOSAGE AND ADMINISTRATION

OPANA ER Tablets are to be swallowed whole and are not to be broken, chewed, dissolved, or crushed. Taking broken, chewed, dissolved, or crushed OPANA ER Tablets leads to rapid release and absorption of a potentially fatal dose of oxymorphone.

Patients must not consume alcoholic beverages, or prescription or non-prescription medications containing alcohol, while on OPANA ER therapy. The co-ingestion of alcohol with OPANA ER may result in increased plasma levels and a potentially fatal overdose of oxymorphone.

OPANA ER is an opioid agonist and a Schedule II controlled substance with an abuse liability similar to morphine and other opioids.

OPANA ER, like morphine and other opioids used in analgesia, can be abused and is subject to criminal diversion.

OPANA ER tablets are to be swallowed whole, and are not to be broken, chewed, crushed or dissolved. Taking broken, chewed, crushed or dissolved OPANA ER tablets leads to the rapid release and absorption of a potentially fatal dose of oxymorphone.

While symmetric (same dose AM and PM), around-the-clock, every 12 hours dosing is appropriate for the majority of patients, some patients may benefit from asymmetric (different dose given in AM than in PM) dosing, tailored to their pain pattern. It is usually appropriate to treat a patient with only one extended-release opioid for around-the-clock therapy.

Selection of patients for treatment with OPANA ER should be governed by the same principles that apply to the use of other extended-release opioid analgesics (see INDICATIONS AND USAGE). As with any opioid drug product, it is necessary to adjust the dosing regimen for each patient individually, taking into account the patient's prior analgesic treatment experience. Physicians should individualize treatment in every case (see DOSAGE AND ADMINISTRATION), using non-opioid analgesics, prn opioids and/or combination products, and chronic opioid therapy in a progressiveplan of pain management such as outlined by the World Health Organization, the American Pain Society and the Federation of State Medical Boards Model Guidelines. Healthcare professionals should follow appropriate pain management principles of careful assessment and ongoing monitoring (see BOXED WARNING).

In the selection of the initial dose of OPANA ER, attention should be given to the following:

1. The total daily dose, potency and specific characteristics of the opioid the patient has been taking previously;
2. The relative potency estimate used to calculate the equivalent oxymorphone dose needed;
3. The patient’s degree of opioid tolerance;
4. The age, general condition, and medical status of the patient;
5. Concurrent non-opioid analgesic and other medications;
6. The type and severity of the patient's pain;
7. The balance between pain control and adverse experiences;
8. Risk factors for abuse, addiction or diversion, including a prior history of abuse, addiction or diversion.

The following dosing recommendations, therefore, can only be considered as suggested approaches to what is actually a series of clinical decisions over time in the management of the pain of each individual patient.

OPANA ER should be administered on an empty stomach, at least one hour prior to or two hours after eating.

Initiation of Therapy
Opioid-Naïve Patients

It is suggested that patients who are not opioid-experienced being initiated on chronic around-the-clock opioid therapy be started with OPANA ER 5 mg every 12 hours. Thereafter, it is recommended that the dose be individually titrated, preferably at increments of 5-10 mg every 12 hours every 3-7 days, to a level that provides adequate analgesia and minimizes side effects under the close supervision of the prescribing physician (see CLINICAL TRIALS: 12-Week Study in Opioid-Naïve Patients with Low Back Pain).

Opioid-Experienced Patients Conversion from OPANA to OPANA ER

Patients receiving OPANA may be converted to OPANA ER by administering half the patient's total daily oral OPANA dose as OPANA ER, every 12 hours. For example, a patient receiving 40 mg/day OPANA may require 20 mg OPANA ER every 12 hours.

Conversion from Parenteral Oxymorphone to OPANA ER

Given the absolute oral bioavailability of approximately 10%, patients receiving parenteral oxymorphone may be converted to OPANA ER by administering 10 times the patient's total daily parenteral oxymorphone dose as OPANA ER in two equally divided doses (e.g., IV dose x 10/2). For example, approximately 20 mg of OPANA ER, every 12 hours, may be required to provide pain relief equivalent to a total daily dose of 4 mg of parenteral oxymorphone. Due to patient variability with regards to opioid analgesic response, upon conversion patients should be closely monitored to ensure adequate analgesia and to minimize side effects.

Conversion from Other Oral Opioids to OPANA ER

For conversion from other opioids to OPANA ER, physicians and other healthcare professionals are advised to refer to published relative potency information, keeping in mind that conversion ratios are only approximate. In general, it is safest to start the OPANA ER therapy by administering half of the calculated total daily dose of OPANA ER (see conversion ratio table below) in 2 divided doses, every 12 hours. The initial dose of OPANA ER can be gradually adjusted until adequate pain relief and acceptable side effects have been achieved. The following table provides approximate equivalent doses, which may be used as a guideline for conversion. The conversion ratios and approximate equivalent doses in this conversion table are only to be used for the conversion from current opioid therapy to OPANA ER. In a Phase 3 clinical trial with an open-label titration period, patients were converted from their current opioid to OPANA ER using the following table as a guide. In general, patients were able to successfully titrate to a stabilized dose of OPANA ER within 4 weeks (see Clinical TRIALS: 12-Week Study in Opioid-Experienced Patients with Low Back Pain). There is substantial patient variation in the relative potency of different opioid drugs and formulations.

CONVERSION RATIOS TO OPANA ER
Approximate Equivalent Dose

Opioid | Oral | Oral Conversion Ratio a
Oxymorphone | 10 mg | 1
Hydrocodone | 20 mg | 0.5
Oxycodone | 20 mg | 0.5
Methadone | 20 mg | 0.5
Morphine | 30 mg | 0.333

a - Ratio for conversion of oral opioid dose to approximate oxymorphone equivalent does. Select opioid and multiply
the dose by the conversion ratio to calculate the approximate oral oxymorphone equivalent.

- The conversion ratios and approximate equivalent doses in this conversion table are only to be used for the conversion from current opioid therapy to Opana ER.
- Sum the total daily dose for the opioid and multiply by the conversion ratio to calculate the oxymorphone total daily dose.
- For patients on a regimen of mixed opioids, calculate the approximate oral oxymorphone dose for each opioid and sum the totals to estimate the total daily oxymorphone dose.
- The dose of OPANA ER can be gradually adjusted, preferably at increments if 10 mg every 12 hours every 3-7 days, until adequate pain relief and acceptable side effects have achieved (see individualization of Dose).

Individualization of Dose

Once therapy is initiated, pain relief and other opioid effects should be frequently assessed. In clinical practice, titration of the total daily OPANA ER dose should be based upon the amount of supplemental opioid utilization, severity of the patient’s pain, and the patient’s ability to tolerate the opioid. Patients should be titrated to generally mild or no pain with the regular use of no more than two doses of supplemental analgesia, i.e. “rescue,” per 24 hours.

If signs of excessive opioid-related adverse experiences are observed, the next dose may be reduced. If this adjustment leads to inadequate analgesia, a supplemental dose of OPANA, another immediate-release opioid, or a non-opioid analgesic may be administered. Dose adjustments should be made to obtain an appropriate balance between pain relief and opioid-related adverse experiences. If significant adverse events occur before the therapeutic goal of mild or no pain is achieved, the events should be treated aggressively. Once adverse events are under control, upward titration should continue to an acceptable level of pain control.

During periods of changing analgesic requirements, including initial titration, frequent contact is recommended between physician, other members of the healthcare team, the patient and the caregiver/family. Patients and caregivers/family members should be advised of the potential side effects.

Patients with Hepatic Impairment

Patients with mild hepatic impairment should be started with the lowest dose and titrated slowly while carefully monitoring side effects. OPANA ER is contraindicated in patients with moderate and severe hepatic dysfunction (see CLINICAL PHARMACOLOGY, CONTRAINDICATIONS and PRECAUTIONS).

Patients with Renal Impairment

There are 57% and 65% increases in oxymorphone bioavailability in patients with moderate and severe renal impairment, respectively (see CLINICAL PHARMACOLOGY and PRECAUTIONS). Accordingly, in patients with creatinine clearance rate less than 50 mL/min, OPANA ER should be started with the lowest dose and titrated slowly while carefully monitoring side effects.

Use with CNS Depressants

OPANA ER, like all opioid analgesics, should be started at 1/3 to 1/2 of the usual dose in patients who are concurrently receiving other central nervous system depressants including sedatives or hypnotics, general anesthetics, phenothiazines, tranquilizers, and alcohol because respiratory depression, hypotension, and profound sedation or coma may result. No specific interaction between oxymorphone and monoamine oxidase inhibitors has been observed, but caution in the use of any opioid in patients taking this class of drugs is appropriate (see PRECAUTIONS: General and PRECAUTIONS: Drug-Drug Interactions).

Geriatrics

The steady-state plasma concentrations of oxymorphone are approximately 40% higher in elderly subjects than in young subjects (see CLINICAL PHARMACOLOGY and PRECAUTIONS). In general, caution should be exercised in the selection of the starting dose of OPANA ER for an elderly patient usually starting at the low end of the dosing range and slowly titrating to adequate analgesia.

Maintenance of Therapy and Supplemental Analgesia

The intent of the titration period is to establish a patient-specific every 12 hours dose that will maintain adequate analgesia with acceptable side effects for as long as pain relief is necessary. During titration and before a stable dose is achieved, OPANA or other immediate-release medications can be used as supplemental analgesia between dosings. Should pain recur, the dose can be incrementally increased to re-establish pain control. The method of therapy adjustment outlined above should be employed to re-establish pain control.

During chronic therapy with OPANA ER, the continued need for around-the-clock opioid therapy should be reassessed periodically.

Cessation of Therapy

When the patient no longer requires therapy with OPANA ER tablets, doses should be tapered gradually to prevent signs and symptoms of withdrawal in the physically dependent patient (see CLINICAL TRIALS: 12-Week Study in Opioid-Naïve Patients with Low Back Pain and CLINICAL TRIALS: 12-Week Study in Opioid-Experienced Patients with Low Back Pain).

SAFETY AND HANDLING

OPANA ER contains oxymorphone, which is a controlled substance. Oxymorphone is controlled under Schedule II of the Controlled Substances Act. Oxymorphone, like all opioids, is liable to diversion and misuse and should be handled accordingly. Patients and their families should be instructed to flush any OPANA ER tablets that are no longer needed.

OPANA ER may be targeted for theft and diversion. Healthcare professionals should contact their State Medical Board, State Board of Pharmacy or State Control Board for information on how to detect or prevent diversion of this product.

Store at 25°C (77°F); excursions permitted to 15°-30°C (59°-86°F). [See USP Controlled Room Temperature].

Dispense in tight container as defined in the USP, with a child-resistant closure (as required).

HOW SUPPLIED

OPANA ER tablets are supplied as follows:

5 mg
Pink, octagon shape, film coated, convex tablets with “E907” over “5” in black print on one side and plain on the other.
Bottles of 100 with child-resistant closure NDC 63481-907-70
Unit-Dose package of 100 tablets (5 blister cards of 20
tablets, not child-resistant, for hospital use only) NDC 63481-907-75

10 mg
Light orange, octagon shape, film coated, convex tablets with “E674” over “10” in black print on one side and plain on the other.
Bottles of 100 with child-resistant closure NDC 63481-674-70
Unit-Dose package of 100 tablets (5 blister cards of 20
tablets, not child-resistant, for hospital use only) NDC 63481-674-75

20 mg
Light green, octagon shape, film coated, convex tablets with “E617” over “20” in black print on one side and plain on the other.
Bottles of 100 with child-resistant closure NDC 63481-617-70
Unit-Dose package of 100 tablets (5 blister cards of 20
tablets, not child-resistant, for hospital use only) NDC 63481-617-75

40 mg
Yellow, octagon shape, film coated, convex tablets with “E693” over “40” in black print on one side and plain on the other.
Bottles of 100 with child-resistant closure NDC 63481-693-70
Unit-Dose package of 100 tablets (5 blister cards of 20
tablets, not child-resistant, for hospital use only) NDC 63481-693-75

Rx Only

CAUTION
DEA Order Form Required.

PATIENT INFORMATION

OPANA® ER (Ō-pan-a)
(Oxymorphone Hydrochloride) Extended-Release Tablets
CII
Rx Only

OPANA ER Tablets, 5 mg
OPANA ER Tablets, 10 mg
OPANA ER Tablets, 20 mg
OPANA ER Tablets, 40 mg

IMPORTANT: Keep OPANA ER in a safe place away from children. Accidental use by a child is a medical emergency and can result in death. If a child accidentally takes OPANA ER, get emergency help right away.

Read the Patient Information that comes with OPANA ER before you start taking it and each time you get a new prescription. There may be new information. This information does not take the place of talking with your healthcare provider about your medical condition or your treatment. Share the important information in this leaflet with members of your household.

What Is the Most Important Information I Should Know About OPANA ER?

- OPANA ER can cause trouble breathing (hypoventilation), which can lead to death, if used differently than the way you were told to use it by your healthcare provider (see “What are the possible side effects of OPANA ER?”).
- Swallow OPANA ER tablets whole. Do not break, crush, dissolve, or chew OPANA ER tablets before swallowing. If a tablet is broken, crushed, dissolved, or chewed, the full 12 hour dose can be taken into your body all at once. This is very dangerous. You could die from an overdose of the medicine. Use OPANA ER exactly the way your healthcare provider prescribes. If you cannot swallow tablets whole, tell your healthcare provider. You may need a different medicine.

What is OPANA ER?

- OPANA ER is a prescription medicine that contains the opioid (narcotic pain medicine) oxymorphone. OPANA ER is used to treat adults with constant pain (around the clock) that is moderate to severe and is expected to last for an extended period of time. OPANA ER is not for occasional (“as needed”) use.
- OPANA ER can cause physical dependence. Do not stop taking OPANA ER all of a sudden if you have been taking it for more than a few days. You could become sick with uncomfortable withdrawal symptoms because your body has become use to the medicine. Talk to your healthcare provider about slowly stopping OPANA ER to avoid getting sick with withdrawal symptoms. Physical dependence is not the same as drug addiction. Your healthcare provider can tell you more about the differences between physical dependence and drug addiction.
- OPANA ER is a controlled substance (CII) because it contains a narcotic painkiller that can be a target for people who abuse prescription medicines or street drugs. Keep your tablets in a safe place to protect them from being stolen. Never give your tablets to anyone else, even if they have the same symptoms you have. Selling or giving away this medicine may harm others, even causing death, and is against the law.

Who Should Not Take OPANA ER?
Do not take OPANA ER if:

- You had surgery within the past day (24 hours) and you were not taking OPANA ER before your surgery.
- Your pain is mild or will go away in a few days.
- Your pain can be controlled by the occasional use of other pain medicines.
- You are having an asthma attack or have severe asthma, trouble breathing, or lung problems.
- You have liver problems.
- You are allergic to OPANA ER or anything in it. See the end of this leaflet for a complete list of ingredients in OPANA ER.

You have had severe allergic reactions to other narcotic pain medicines (such as morphine or codeine medicines). A severe allergic reaction includes a severe rash, hives, breathing problems, or dizziness.

OPANA ER is not for children under 18 years of age.

What Should I Tell My Healthcare Provider Before Starting OPANA ER?
Tell your healthcare provider about all of your medical problems, especially if you:

- have trouble breathing or lung problems
- have a head injury or brain problem
- have liver or kidney problems
- have adrenal gland problems, such as Addison’s disease
- have convulsions or seizures
- have thyroid problems
- have problems urinating or prostate problems
- have pancreas problems
- have a drinking problem or alcoholism
- have severe mental problems or hallucinations (see or hear things that are not really there)
- have past or present drug abuse or drug addiction problems
- are pregnant or plan to become pregnant. OPANA ER may harm your unborn baby.
- are breastfeeding. OPANA ER may pass through your milk and may harm your baby. You should not breastfeed while taking OPANA ER.

Tell your healthcare provider about all the medicines you take, including prescription and nonprescription medicines, vitamins, and herbal supplements. Some medicines may cause serious problems when taken with OPANA ER, especially if they cause sleepiness (like sleeping pills, anxiety medicines, antihistamines, or tranquilizers).

Do not take any new medicines while using OPANA ER until you have talked to your healthcare provider or pharmacist and they have told you it is safe.

Know the medicines you take. Keep a list of them to show your healthcare provider and pharmacist.

How Should I Take OPANA ER?

- Follow your healthcare provider’s directions exactly. Your healthcare provider may change your dose based on your reactions to the medicine. Do not change your dose unless your healthcare provider tells you to change it. Do not take OPANA ER more often than prescribed.
- Swallow OPANA ER tablets whole. Do not break, crush, dissolve, or chew OPANA ER tablets before swallowing. If a tablet is broken, crushed, dissolved, or chewed, the full 12 hour dose can be taken into your body all at once. This is very dangerous. You could die from an overdose of the medicine. If you cannot swallow tablets whole, tell your healthcare provider. You may need a different medicine.
- Take OPANA ER every 12 hours or as instructed by your healthcare provider. OPANA ER should be taken on an empty stomach, at least one hour before or two hours after meals. Talk to your healthcare provider if you feel sick taking OPANA ER on an empty stomach.
- If you miss a dose, take it as soon as possible. If it is almost time for your next dose, skip the missed dose and go back to your regular dosing schedule. Do not take 2 doses at once unless your healthcare provider tells you to. If you are not sure about your dosing call your healthcare provider.
- If you take too much OPANA ER or overdose, call your local emergency number or poison control center right away.
- Talk to your healthcare provider often about your pain. Your healthcare provider can decide if you still need OPANA ER.
- If you have side effects that bother you or if you continue to have pain, call your healthcare provider.
- Stopping OPANA ER. If your healthcare provider decides you no longer need OPANA ER, ask how to slowly reduce the dose of your medicine so you don’t get uncomfortable (withdrawal) symptoms such as nausea, sweating, and pain. You should not stop taking OPANA ER all at once if you have been taking it for more than a few days without talking to your healthcare provider. OPANA ER can cause physical dependence. You can get sick with withdrawal symptoms if you stop OPANA ER all at once, because your body has become use to it.

After you stop taking OPANA ER, flush the unused tablets down the toilet. Safely dispose of OPANA ER out of the reach of children and pets.

What Should I Avoid While Taking OPANA ER?

- Do not drive, operate heavy machinery, or participate in any other possibly dangerous activities until you know how you react to this medicine. OPANA ER can make you sleepy. Ask your healthcare provider to tell you when it is okay to do these activities.
- Do not drink alcohol while using OPANA ER. It may increase the chance of having dangerous side effects including overdose and death.

What are the Possible Side Effects of OPANA ER?
OPANA ER can cause trouble breathing.
Call your healthcare provider or get medical help right away if:

- your breathing slows down
- you have shallow breathing (little chest movement with breathing)
- you feel faint, dizzy, confused, or have any other unusual symptoms

These can be signs that you have taken too much OPANA ER (overdose) or the dose is too high for you, which can be dangerous and lead to death if not treated.

OPANA ER can cause your blood pressure to drop. This can make you feel dizzy if you get up too fast from sitting or lying down. Low blood pressure is also more likely to happen if you are taking other medicines that can also lower your blood pressure.

OPANA ER can cause physical dependence. Your body will get used to OPANA ER if you take it more than a few days. You can get sick with withdrawal symptoms if you stop taking OPANA ER all at once. You can avoid getting sick with withdrawal symptoms by stopping OPANA ER slowly. Your healthcare provider will tell you how to do this.

There is a chance of abuse or addiction with OPANA ER. Abuse or addiction is different than a physical dependence. If you have abused prescription medicines, street drugs or alcohol in the past, you may have a higher chance of developing abuse or addiction again while using OPANA ER. If you have more concerns, talk to your healthcare provider for more information about abuse and addiction.

The most common side effects of OPANA ER are nausea, constipation, dizziness, vomiting, itching, sleepiness, headache, increased sweating, and sedation. Some of these side effects may decrease with continued use. Talk to your healthcare provider if you continue to have these side effects.

These are not all the possible side effects of OPANA ER. For a complete list, ask your healthcare provider or pharmacist.

Constipation (decrease in the usual number of hard bowel movements) is a common side effect of opioid medicines, including OPANA ER. Talk to your healthcare provider or pharmacist about the use of laxatives (medicines to treat constipation) and stool softeners to prevent or treat constipation while taking OPANA ER.

How should I store OPANA ER?

- Store OPANA ER at room temperature between 59° to 86°F (15° to 30°C).
- Keep OPANA ER in a childproof container and store in a safe place to protect it from being stolen.
- Keep OPANA ER out of the reach of children. Accidental overdose in children is an emergency and can result in death.

General Information about OPANA ER

- Do not use OPANA ER for conditions for which it was not prescribed.
- Do not give OPANA ER to other people, even if they have the same symptoms you have. It may harm them, even causing death, and it is against the law.

This leaflet summarizes the most important information about OPANA ER. If you would like more information, talk with your healthcare provider. Also, you can ask your pharmacist or healthcare provider for information about OPANA ER that is written for healthcare professionals.

For additional information, please go to www.Endo.com or www.opana.com

What are the ingredients in OPANA ER?
Active Ingredient: oxymorphone hydrochloride
Inactive Ingredients: hypromellose, iron oxide black, methylparaben, propylene glycol, silicified microcrystalline cellulose, sodium stearyl fumarate, TIMERx®-N, titanium dioxide, and triacetin. The 5 mg, 10 mg and 20 mg tablets also contain macrogol, and polysorbate 80. In addition, the 5 mg tablets contain iron oxide red. The 10 mg tablets contain FD and C yellow No. 6. The 20 mg tablets contain FD and C blue No. 1, FD and C yellow No. 6, and D and C yellow No. 10. The 40 mg tablets contain FD and C yellow No. 6, D and C yellow No.10, and lactose monohydrate.

CAUTION: Federal law prohibits dispensing without prescription.

Manufactured for:
Endo Pharmaceuticals Inc.
Chadds Ford, Pennsylvania 19317

Manufactured by:
Novartis Consumer Health Inc.
Lincoln, NE 68517

TIMERx®-N is a registered Trademark of Penwest Pharmaceuticals Co., Danbury, Connecticut and is used herein pursuant to a license agreement between Penwest and Endo Pharmaceuticals.

Copyright © Endo Pharmaceuticals Inc. 2006

413442/June, 2006

PACKAGE LABEL

OPANA ER C-II 5 MG TABLETS

OPANA ER C-II 10 MG TABLETS

OPANA ER C-II 40 MG TABLETS